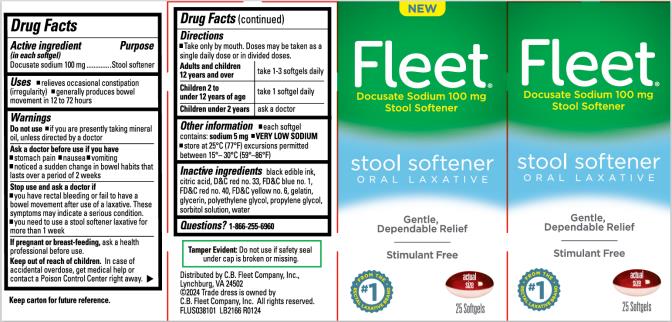 DRUG LABEL: Fleet
NDC: 0132-0402 | Form: CAPSULE, LIQUID FILLED
Manufacturer: C.B. Fleet Company, Inc.
Category: otc | Type: HUMAN OTC DRUG LABEL
Date: 20240627

ACTIVE INGREDIENTS: DOCUSATE SODIUM 100 mg/1 1
INACTIVE INGREDIENTS: CITRIC ACID MONOHYDRATE; D&C RED NO. 33; FD&C BLUE NO. 1; FD&C RED NO. 40; FD&C YELLOW NO. 6; GLYCERIN; GELATIN; POLYETHYLENE GLYCOL, UNSPECIFIED; SORBITOL SOLUTION; WATER; PROPYLENE GLYCOL

Fleet Oral Lax Docusate sodium 0132-0402

Active ingredient (in each softgel)

Docusate sodium 100 mg

Purpose

Stool softener

Uses

- relieves occasional constipation (irregularity)
- generally produces bowel movement in 12 to 72 hours

Warnings

Do not use

- if you are presently taking mineral oil, unless directed by a doctor

Ask a doctor before use if you have

- abdominal pain
- nausea
- vomiting
- noticed a sudden change in bowel habits that lasts over a period of 2 weeks

Stop use and ask a doctor if

- you have rectal bleeding or fail to have a bowel movement after use of a laxative. These symptoms may indicate a serious condition.
- you need to use a stool softener laxative for more than 1 week

If pregnant or breast-feeding,

ask a health professional before use.

Keep out of reach of children.

In case of accidental overdose, get medical help or contact a Poison Control Center right away.

Directions

- Take only by mouth. Doses may be taken as a single daily dose or in divided doses.

Adults and children 12 years and over | take 1-3 softgels daily
Children 2 to under 12 years of age | take 1 softgel daily
Children under 2 years | ask a doctor

Other information

- each softgel contains: sodium 5 mg
- VERY LOW SODIUM
- store at 25°C (77°F) excursions permitted between 15°– 30°C (59°–86°F)

Inactive ingredients

black edible ink, citric acid, D&C red no. 33, FD&C blue no. 1, FD&C red no. 40, FD&C yellow no. 6, gelatin, glycerin, polyethylene glycol, propylene glycol, sorbitol solution, water

Questions?

Call 1-866-255-6960

Principal Display Panel

Fleet

Docusate sodium 100 mg Stool Softener

Oral Laxative

25 softgels